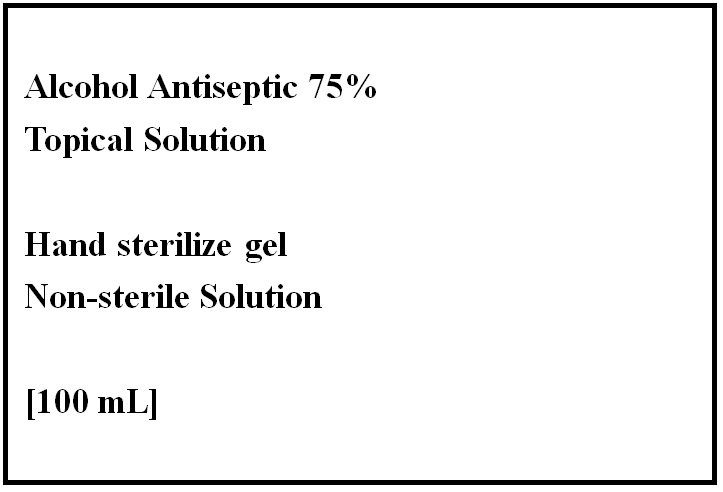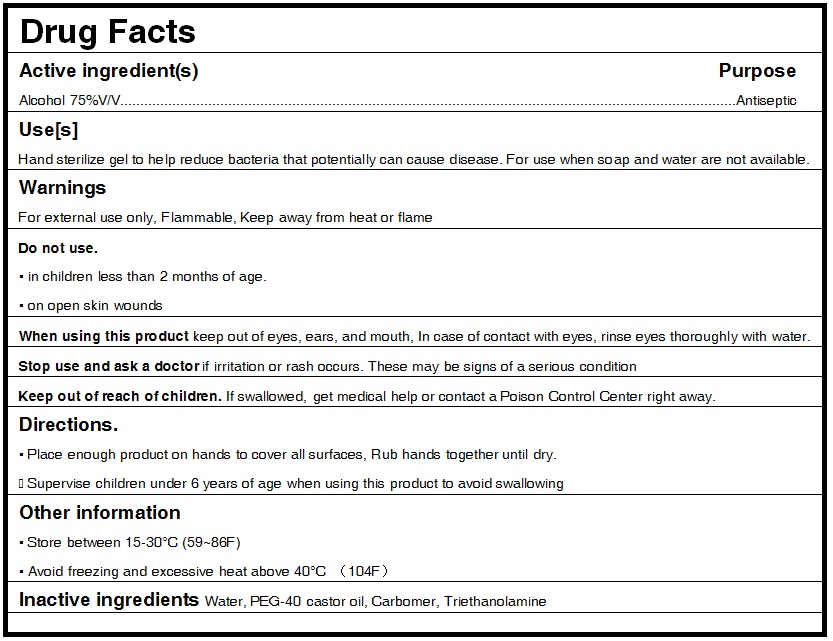 DRUG LABEL: Hand Sanitizer
NDC: 75234-237 | Form: GEL
Manufacturer: Shantou Aoxiangqi Daily Chemical Co., Ltd.
Category: otc | Type: HUMAN OTC DRUG LABEL
Date: 20200412

ACTIVE INGREDIENTS: ALCOHOL 75 mL/100 mL
INACTIVE INGREDIENTS: TROLAMINE 0.4 mL/100 mL; CARBOMER HOMOPOLYMER, UNSPECIFIED TYPE 0.4 mL/100 mL; PEG-40 CASTOR OIL 0.15 mL/100 mL; WATER 24.05 mL/100 mL

Purpose

Antiseptic, Hand Sanitizer

Use

Hand sterilize gel to help reduce bacteria that potentially can cause disease. For use when soap and water are not available.

Warnings

For external use only. Flammable. Keep away from heat or flame

Do not use

- in children less than 2 months of age
- on open skin wounds

When using this product keep out of eyes, ears, and mouth. In case of contact with eyes, rinse eyes thoroughly with water.

Stop use and ask a doctor if irritation or rash occurs. These may be signs of a serious condition.

Keep out of reach of children. If swallowed, get medical help or contact a Poison Control Center right away.

Directions

- Place enough product on hands to cover all surfaces. Rub hands together until dry.
- Supervise children under 6 years of age when using this product to avoid swallowing.

Other information

- Store between 15-30°C (59-86°F)
- Avoid freezing and excessive heat above 40°C (104°F)

Inactive ingredients

Water, PEG-40 castor oil, Carbomer, Triethanolamine

Package Label - Principal Display Panel

60 ml NDC: 75234-237-01

100 ml NDC: 75234-237-02

250 ml NDC: 75234-237-03

300 ml NDC: 75234-237-04

500 ml NDC: 75234-237-05

800 ml NDC: 75234-237-06

1000 ml NDC: 75234-237-07